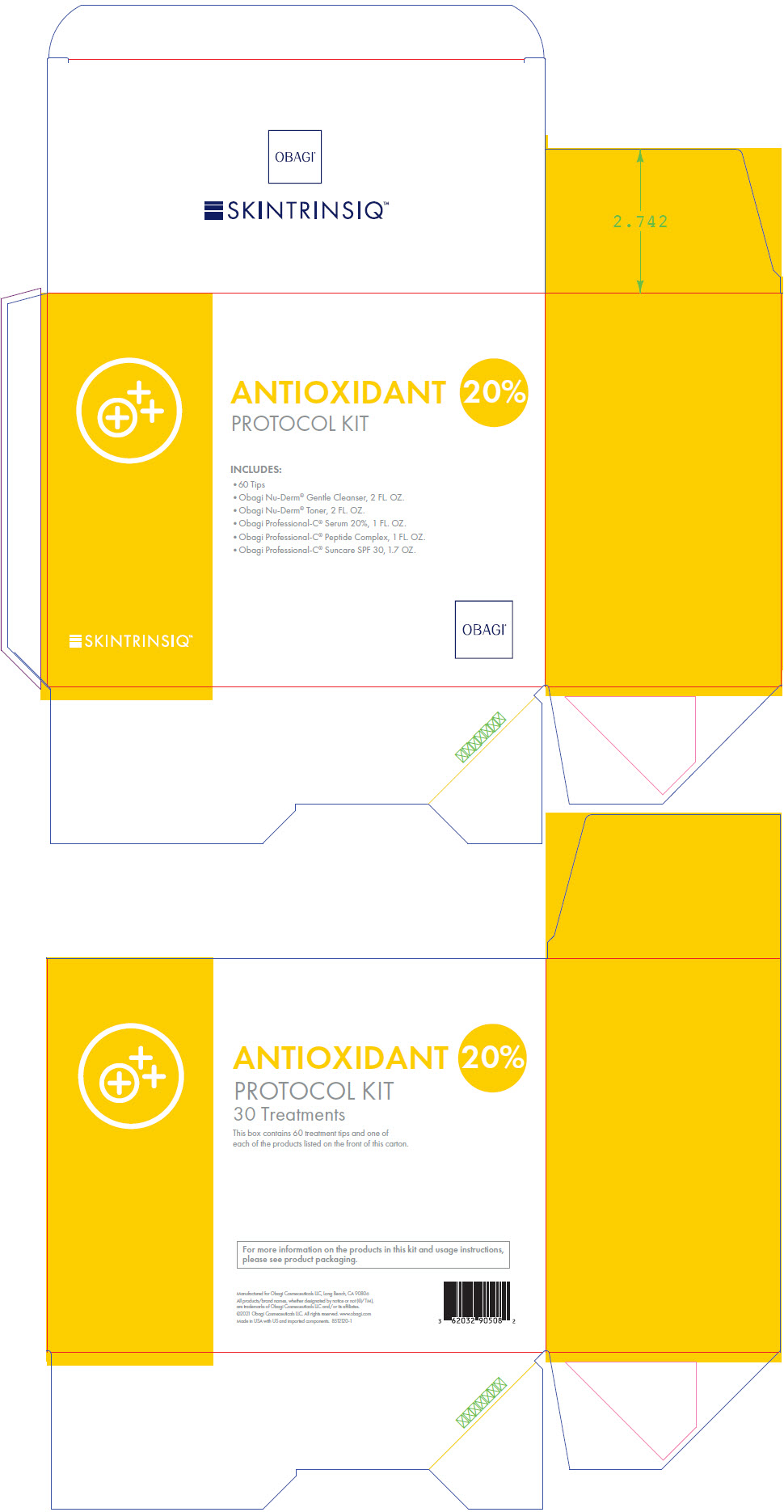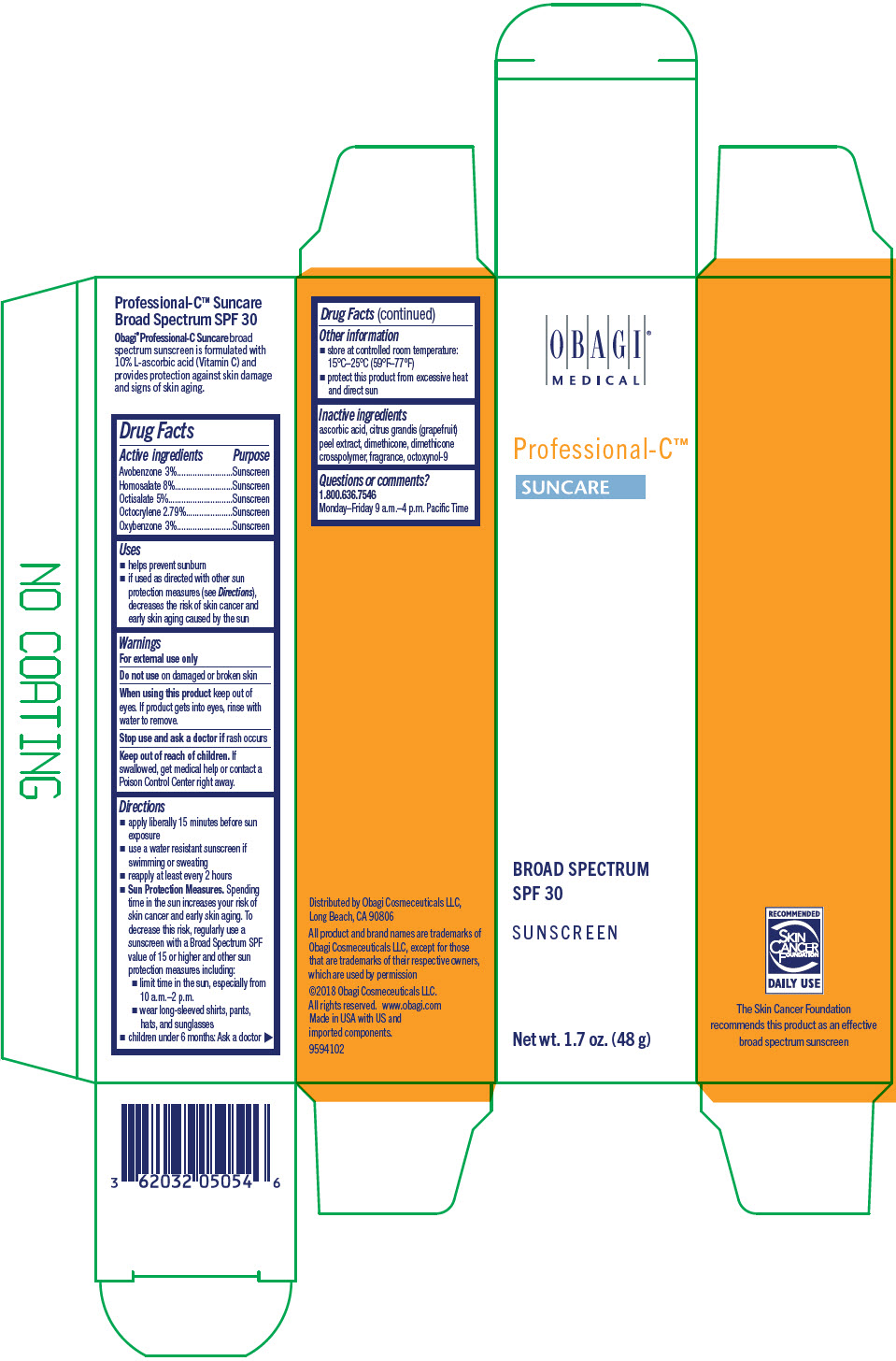 DRUG LABEL: Obagi Skintrinsiq Antioxidant Protocol
NDC: 62032-908 | Form: KIT | Route: TOPICAL
Manufacturer: Obagi Cosmeceuticals LLC
Category: otc | Type: HUMAN OTC DRUG LABEL
Date: 20250321

ACTIVE INGREDIENTS: AVOBENZONE 30 mg/1 g; HOMOSALATE 80 mg/1 g; OCTISALATE 50 mg/1 g; OCTOCRYLENE 27.9 mg/1 g; OXYBENZONE 30 mg/1 g
INACTIVE INGREDIENTS: ASCORBIC ACID; CITRUS MAXIMA FRUIT RIND; DIMETHICONE, UNSPECIFIED; DIMETHICONE CROSSPOLYMER; OCTOXYNOL-9

Obagi ® Skintrinsiq™ Antioxidant Protocol Kit 20%

Obagi® Professional-C™ Suncare SPF 30

Drug Facts

ACTIVE INGREDIENT

Active ingredients | Purpose
Avobenzone 3% | Sunscreen
Homosalate 8% | Sunscreen
Octisalate 5% | Sunscreen
Octocrylene 2.79% | Sunscreen
Oxybenzone 3% | Sunscreen

Uses

- helps prevent sunburn
- if used as directed with other sun protection measures (see Directions), decreases the risk of skin cancer and early skin aging caused by the sun

Warnings

For external use only

Do not use on damaged or broken skin

When using this product keep out of eyes. If product gets into eyes, rinse with water to remove.

Stop use and ask a doctor if rash occurs

Keep out of reach of children. If swallowed, get medical help or contact a Poison Control Center right away.

Directions

- apply liberally 15 minutes before sun exposure
- use a water resistant sunscreen if swimming or sweating
- reapply at least every 2 hours
- Sun Protection Measures. Spending time in the sun increases your risk of skin cancer and early skin aging. To decrease this risk, regularly use a sunscreen with a Broad Spectrum SPF value of 15 or higher and other sun protection measures including:
  - limit time in the sun, especially from 10 a.m.–2 p.m.
  - wear long-sleeved shirts, pants, hats, and sunglasses
- children under 6 months: Ask a doctor

Other information

- store at controlled room temperature: 15°C–25°C (59°F–77°F)
- protect this product from excessive heat and direct sun

Inactive ingredients

ascorbic acid, citrus grandis (grapefruit) peel extract, dimethicone, dimethicone crosspolymer, fragrance, octoxynol-9

Questions or comments?

1.800.636.7546

Monday–Friday 9 a.m.–4 p.m. Pacific Time

Distributed by Obagi Cosmeceuticals LLC,
Long Beach, CA 90806

PRINCIPAL DISPLAY PANEL - Kit Carton

SKINTRINSIQ™

ANTIOXIDANT 20%

PROTOCOL KIT

INCLUDES:

- 60 Tips
- Obagi Nu-Derm® Gentle Cleanser, 2 FL. OZ.
- Obagi Nu-Derm® Toner, 2 FL. OZ.
- Obagi Professional-C® Serum 20%, 1 FL. OZ.
- Obagi Professional-C® Peptide Complex, 1 FL. OZ.
- Obagi Professional-C® Suncare SPF 30, 1.7 OZ.

OBAGI®

PRINCIPAL DISPLAY PANEL - 48 g Bottle Carton

OBAGI®
MEDICAL

Professional-C™

SUNCARE

BROAD SPECTRUM
SPF 30

SUNSCREEN

Net wt. 1.7 oz. (48 g)